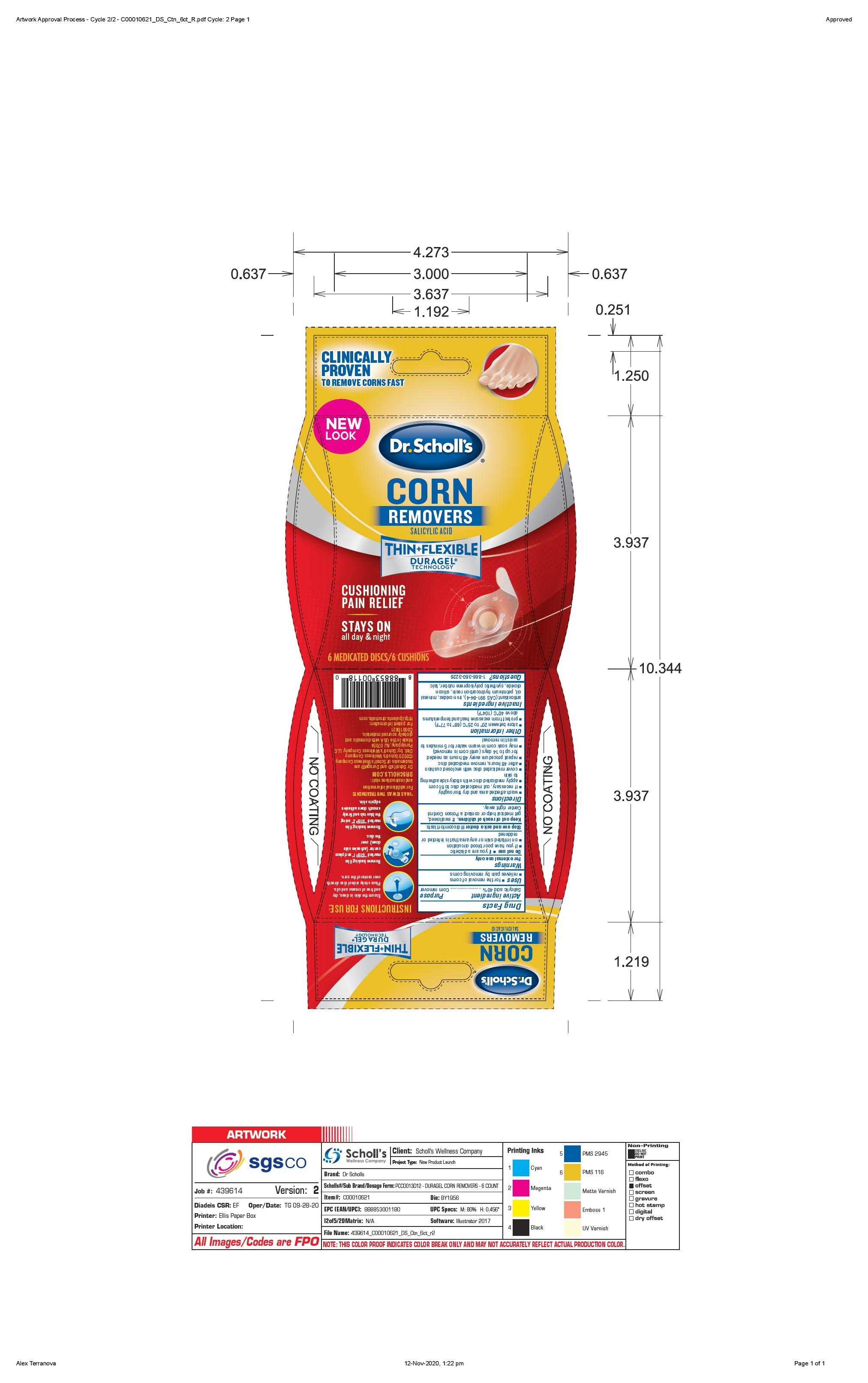 DRUG LABEL: Scholls Wellness Company LLC
NDC: 73469-0627 | Form: DISC
Manufacturer: Scholls Wellness Company LLC
Category: otc | Type: HUMAN OTC DRUG LABEL
Date: 20251221

ACTIVE INGREDIENTS: SALICYLIC ACID 0.4 g/1 g
INACTIVE INGREDIENTS: ANTIOXIDANT GS; BROWN IRON OXIDE; MINERAL OIL; TALC; WHITE PETROLATUM; SILICON DIOXIDE

Duragel Corn Remover

Drug Facts

ACTIVE INGREDIENT

Salicylic Acid 40%..........Corn Remover

Purpose

Corn Remover

Uses

for the removal of corns

relieves pain by removing corns

Warnings

For external use only

Do not use

if you are a diabetic

if you have poor blood circulation

on irritated skin or any area that is infected or reddened

Stop use and ask a doctor if discomfort lasts

Keep out of reach of children. If swallowed, get medical help or contact Poison Control Center right away.

Directions

wash affected area and dry thoroughly

if necessary, cut medicated disc to fit corn

apply medicated disc with sticky side adhering to skin

cover medicated disc with enclosed cushion

after 48 hours, remove medicated disc

repeat procedure every 48 hours as needed for up to 14 days (untl corn is removed)

may soak corn in warn water for 5 minutes to assist in removal

Other Information

store between 20º to 25ºC (68º to 77ºF)

protect from excessive heat and temperatures above 40ºC (104ºF)

INACTIVE INGREDIENT

Inactive ingredients antioxidant (CAS 991-84-4), iron oxides, mineral oil, petroleum hydrocarbon resin, silicon dioxide, synthetic polyisoprene rubber, talc

Questions? 1-866-360-3226